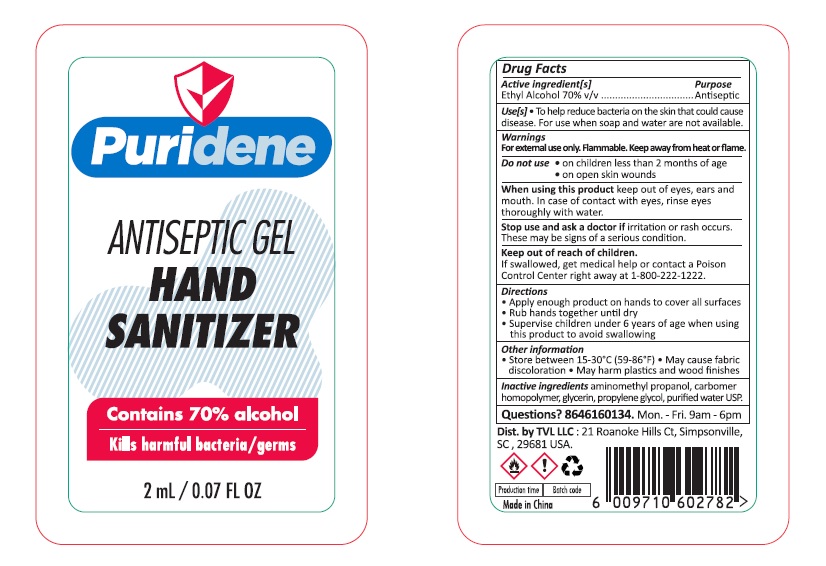 DRUG LABEL: Puridene HAND SANITIZER
NDC: 74542-015 | Form: GEL
Manufacturer: Ningbo SKL International Co.,Ltd.
Category: otc | Type: HUMAN OTC DRUG LABEL
Date: 20200828

ACTIVE INGREDIENTS: ALCOHOL 70 mL/100 mL
INACTIVE INGREDIENTS: WATER; PROPYLENE GLYCOL; AMINOMETHYLPROPANOL; CARBOMER HOMOPOLYMER, UNSPECIFIED TYPE; GLYCERIN

Puridene

Active Ingredient

Alcohol 70% v/v

Purpose

Antiseptic

Uses

To help reduce bacteria on the skin that could cause disease. For use then soap and water are unavailable.

Warnings

For external use only
Flammable
Keep away from fire or flame

Do not use:

- On the children less than 2 months of age
- On open skin wounds

When using this product:

- Keep out of eyes,ears and mouth.
- In case of contact with eyes, rinse eyes thoroughly with water

Stop use and ask a doctor if:

- Irritation, rash occurs. These may be signs of a serious condition

Keep out of reach of children

If swallowed, seek medical help or contact a Poison Control Center right away at 1-800-222-1222

Directions

- Apply enough product on hands to cover all surfaces.
- Rub hands together until dry.
- Supervise children under 6 years of age when using this product to avoid swallowing.

Other Information

- Store between 15-30℃(59-86℉).
- May cause fabric discoloration.
- May harm plastic and wood finishes.

Inactive Ingredient

Aminomethyl propanol, carbomer homopolymer, glycerin, propylene glycol, purified water USP

Questions? 8646160134 Mon. - Fri. 9am-6pm